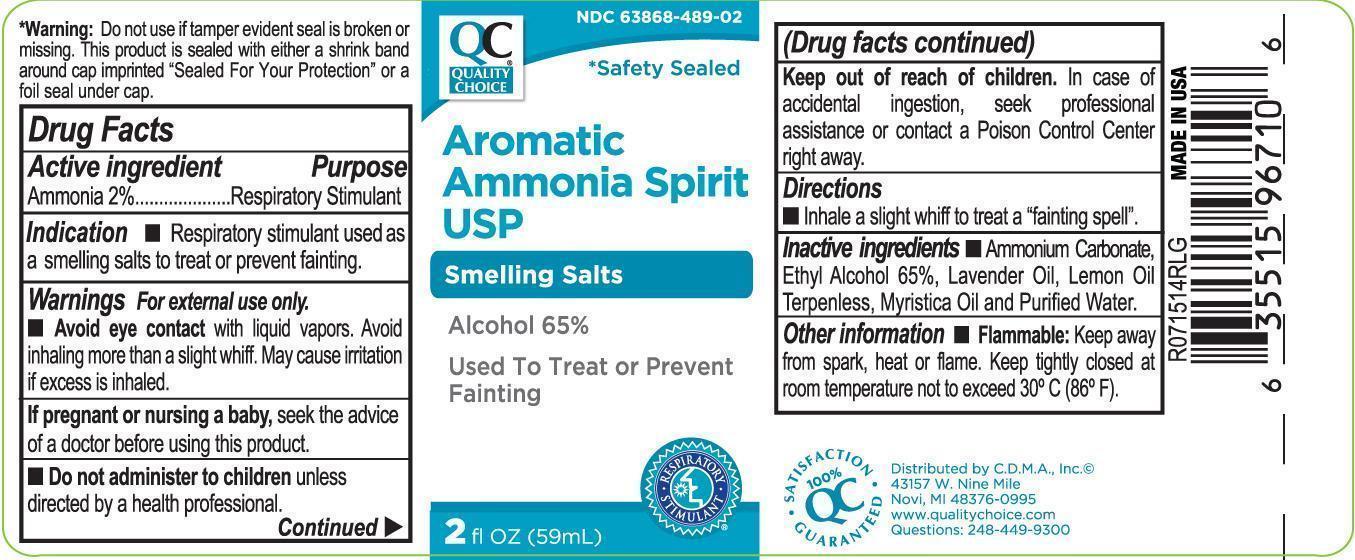 DRUG LABEL: Quality Choice Aromatic Ammonia Spirit
NDC: 63868-489 | Form: LIQUID
Manufacturer: Chain Drug Market Association
Category: otc | Type: HUMAN OTC DRUG LABEL
Date: 20201219

ACTIVE INGREDIENTS: AMMONIA 20 mg/1 mL
INACTIVE INGREDIENTS: AMMONIUM CARBONATE; ALCOHOL; LAVENDER OIL; LEMON OIL, TERPENELESS; WATER

Quality Choice Aromatic Ammonia Spirit

Drug Facts

Active Ingredient

Ammonia 2 %

Purpose

Respiratory Stimulant

Indication

Respiratory stimulant used as a smelling salts to treat or prevent fainting.

Warnings

For external use only. Avoid eye contact with liquid vapors. Avoid inhaling more than a slight whiff. May cause irritation if excess is inhaled.

If pregnant or nursing a baby

seek the advice of a doctor before using this product.

Keep out of the reach of children

In case of accidental ingestion, seek professional assistance or contact a Poison Control Center right away.

Directions

Inhale a slight whiff to treat a "faining spell"

Inactive Ingredients

Ammonium Carbonate, Ethyl Alcohol 656%, Lavender Oil, Lemon Oil Terpenless, Myristica Oil and Purified Water.

Other Information

Flammable: Keep away from spark, heat or flame. Keep tightly closed at room temperature not toexceed 30C (86F).